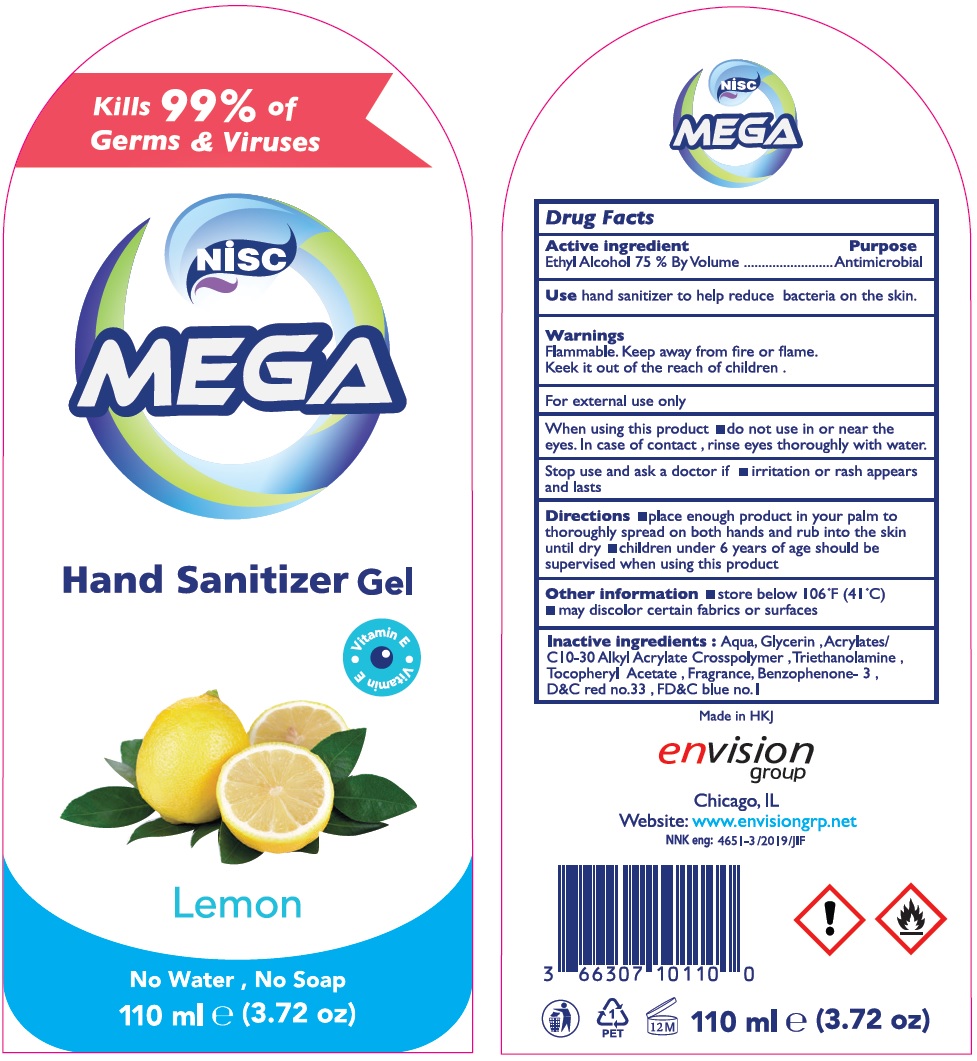 DRUG LABEL: NISC MEGA Hand Sanitizer Gel
NDC: 75771-006 | Form: GEL
Manufacturer: NOWREZ & ISMAIL SHUKRI COMPANY
Category: otc | Type: HUMAN OTC DRUG LABEL
Date: 20200804

ACTIVE INGREDIENTS: ALCOHOL 75 mL/100 mL
INACTIVE INGREDIENTS: WATER; GLYCERIN; CARBOMER INTERPOLYMER TYPE A (ALLYL SUCROSE CROSSLINKED); TROLAMINE; .ALPHA.-TOCOPHEROL ACETATE; OXYBENZONE; D&C RED NO. 33; FD&C BLUE NO. 1

Nisc MEGA Hand Sanitizer Gel

Active ingredient

Ethyl Alcohol 75 % By Volume

Purpose

Antimicrobial

Use

hand sanitizer to help reduce bacteria on the skin.

Warnings

Flammable, Keep away from fire or flame.

For external use only

When using this product ■ do not use in or near the eyes. In case of contact, rinse eyes thoroughly with water.

Stop use and ask a doctor if ■ irritation or rash appears and lasts

Keep it out of the reach of children.

Directions

■ place enough product in your palm to thoroughly spread on both hands and rub into the skin until dry. ■ children under 6 years of age should be supervised when using this product

Other information

■ store below 106 °F (41 °C)

■ may discolor certain fabrics or surfaces

Inactive ingredients :

Aqua, Glycerin, Acrylates/C10-30 Alkyl Acrylate Crosspolymer, Triethanolamine, Tocopheryl Acetate, Fragrance, Benzophenone- 3, D&C red no.33, FD&C blue no. 1

Kills 99% of Germs & Viruses

Vitamin E

Lemon

No Water, No Soap

Made in HKJ

envision group

Chicago, IL

Website: www. envisiongrp.net